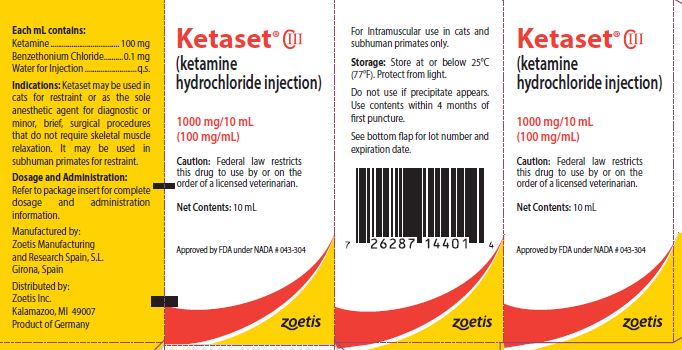 DRUG LABEL: Ketaset
NDC: 54771-2013 | Form: INJECTION
Manufacturer: Zoetis Inc.
Category: animal | Type: PRESCRIPTION ANIMAL DRUG LABEL
Date: 20191001
DEA Schedule: CIII

ACTIVE INGREDIENTS: KETAMINE HYDROCHLORIDE 100 mg/1 mL
INACTIVE INGREDIENTS: BENZETHONIUM CHLORIDE 0.1 mg/1 mL

Ketaset® CIII
(ketamine hydrochloride injection)

Veterinary Injection For Intramuscular Use in Cats and Subhuman Primates Only

CAUTION

Federal law restricts this drug to use by or on the order of a licensed veterinarian.

DESCRIPTION

KETASET (ketamine hydrochloride injection) is a rapid-acting, nonnarcotic, nonbarbiturate agent for anesthetic use in cats and for restraint in subhuman primates. It is chemically designated dl 2-(o-chlorophenyl)-2-(methylamino) cyclohexanone hydrochloride and is supplied as a slightly acid (pH 3.5 to 5.5) solution for intramuscular injection in a concentration containing the equivalent of 100 mg ketamine base per milliliter and contains not more than 0.1 mg/mL benzethonium chloride as a preservative.

INDICATIONS

KETASET may be used in cats for restraint or as the sole anesthetic agent for diagnostic or minor, brief, surgical procedures that do not require skeletal muscle relaxation. It may be used in subhuman primates for restraint.

DOSAGE AND ADMINISTRATION

KETASET is well tolerated by cats and subhuman primates when administered by intramuscular injection.

Fasting prior to induction of anesthesia or restraint with KETASET is not essential; however, when preparing for elective surgery, it is advisable to withhold food for at least six hours prior to administration of KETASET.

Anesthesia may be of shorter duration in immature cats. Restraint in subhuman primate neonates (less than 24 hours of age) is difficult to achieve.

As with other anesthetic agents, the individual response to KETASET is somewhat varied depending upon the dose, general condition and age of the subject so that dosage recommendations cannot be absolutely fixed.

Dosage

Cats: A dose of 11 mg/kg (5 mg/lb) is recommended to produce restraint.

Dosages from 22 to 33 mg/kg (10 to 15 mg/lb) produce anesthesia that is suitable for diagnostic or minor surgical procedures that do not require skeletal muscle relaxation.

Subhuman Primates: The recommended restraint dosages of KETASET (ketamine hydrochloride injection, USP) for the following species are: Cercocebus torquatus (white-collared mangabey), Papio cynocephalus (yellow baboon), Pan troglodytes verus (chimpanzee), Papio anubis (olive baboon), Pongo pygmaeus (orangutan), Macaca nemestrina (pig-tailed macaque) 5 to 7.5 mg/kg; Presbytis entellus (entellus langur) 3 to 5 mg/kg; Gorilla gorilla gorilla (gorilla) 7 to 10 mg/kg; Aotus trivirgatus (night monkey) 10 to 12 mg/kg; Macaca mulatta (rhesus monkey) 5 to 10 mg/kg; Cebus capucinus (white-throated capuchin) 13 to 15 mg/kg; and Macaca fascicularis (crabeating macaque), Macaca radiata (bonnet macaque) and Saimiri sciureus (squirrel monkey) 12 to 15 mg/kg.

A single intramuscular injection produces restraint suitable for TB testing; radiography, physical examination or blood collection.

CONTRAINDICATIONS

KETASET is contraindicated in cats and subhuman primates suffering from renal or hepatic insufficiency.

KETASET is detoxified by the liver and excreted by the kidneys; therefore, any preexistent hepatic or renal pathology or impairment of function can be expected to result in prolonged anesthesia; related fatalities have been reported.

PRECAUTIONS

In cats, doses in excess of 50 mg/kg during any single procedure should not be used. The maximum recommended dose in subhuman primates is 40 mg/kg.

To reduce the incidence of emergence reactions, animals should not be stimulated by sound or handling during the recovery period. However, this does not preclude the monitoring of vital signs.

Apnea, respiratory arrest, cardiac arrest and death have occasionally been reported with ketamine used alone, and more frequently when used in conjunction with sedatives or other anesthetics. Close monitoring of patients is strongly advised during induction, maintenance and recovery from anesthesia.

Color of solution may vary from colorless to very slightly yellowish and may darken upon prolonged exposure to light. This darkening does not affect potency. Do not use if precipitate appears.

ADVERSE REACTIONS

Respiratory depression may occur following administration of high doses of KETASET (ketamine hydrochloride injection, USP). If at any time respiration becomes excessively depressed and the animal becomes cyanotic, resuscitative measures should be instituted promptly. Adequate pulmonary ventilation using either oxygen or room air is recommended as a resuscitative measure.

Adverse reactions reported have included emesis, salivation, vocalization, erratic recovery and prolonged recovery, spastic jerking movements, convulsions, muscular tremors, hypertonicity, opisthotonos, dyspnea and cardiac arrest.

In the cat, myoclonic jerking and/or mild tonic convulsions can be controlled by ultrashort-acting barbiturates which should be given to effect. The barbiturates should be administered intravenously at a dose level of one-sixth to one-fourth the usual dose for the product being used.

Acepromazine may also be used. However, recent information indicates that some phenothiazine derivatives may potentiate the toxic effects of organic phosphate compounds such as found in flea collars and certain anthelmintics. A study has indicated that ketamine hydrochloride alone does not potentiate the toxic effects of organic phosphate compounds.

To report suspected adverse reactions, to obtain a Material Safety Data Sheet or for technical assistance, call 1-888-963-8471.

ACTION

KETASET is a rapid-acting agent whose pharmacological action is characterized by profound analgesia, normal pharyngeal-laryngeal reflexes, mild cardiac stimulation and respiratory depression. Skeletal muscle tone is variable and may be normal, enhanced or diminished. The anesthetic state produced does not fit into the conventional classification of stages of anesthesia, but instead KETASET produces a state of unconsciousness which has been termed "dissociative" anesthesia in that it appears to selectively interrupt association pathways to the brain before producing somesthetic sensory blockade.

In contrast to other anesthetics, protective reflexes, such as coughing and swallowing are maintained under KETASET anesthesia. The degree of muscle tone is dependent upon level of dose; therefore, variations in body temperature may occur. At low dosage levels there may be an increase in muscle tone and a concomitant slight increase in body temperature. However, at high dosage levels there is some diminution in muscle tone and a resultant decrease in body temperature, to the point where supplemental heat may be advisable.

In cats, there is usually some transient cardiovascular stimulation, increased cardiac output with slight increase in mean systolic pressure with little or no change in total peripheral resistance. At higher doses the respiratory rate is usually decreased.

The assurance of a patent airway is greatly enhanced by virtue of maintained pharyngeal-laryngeal reflexes. Although some salivation is occasionally noted, the persistence of the swallowing reflex aids in minimizing the hazards associated with ptyalism. Salivation may be effectively controlled with atropine sulfate in dosages of 0.04 mg/kg (0.02 mg/lb) in cats and 0.01 to 0.05 mg/kg (0.005 to 0.025 mg/lb) in subhuman primates.

Other reflexes, e.g., corneal, pedal, etc., are maintained during KETASET anesthesia, and should not be used as criteria for judging depth of anesthesia. The eyes normally remain open with the pupils dilated. It is suggested that a bland ophthalmic ointment be applied to the cornea if anesthesia is to be prolonged.

Following administration of recommended doses, cats become ataxic in about 5 minutes with anesthesia usually lasting from 30 to 45 minutes at higher doses. At the lower doses, complete recovery usually occurs in 4 to 5 hours but with higher doses recovery time is more prolonged and may be as long as 24 hours.

In studies involving 14 species of subhuman primates represented by at least 10 anesthetic episodes for each species, the median time to restraint ranged from 1.5 [Aotus trivirgatus (night monkey) and Cebus capucinus (white-throated capuchin)] to 5.3 minutes [Macaca nemestrina (pig-tailed macaque)]. The median duration of restraint ranged between 20 and 55 minutes in all but five of the species studied. Total time from injection to end of restraint ranged from 43 [Saimiri sciureus (squirrel monkey)] to 183 minutes [Macaca nemestrina (pig-tailed macaque)] after injection. Recovery is generally smooth and uneventful. The duration is dose related.

By single intramuscular injection, KETASET usually has a wide margin of safety in cats and subhuman primates. In cats, cases of prolonged recovery and death have been reported.

CLINICAL STUDIES

KETASET has been clinically studied in subhuman primates in addition to those species listed under Administration and Dosage. Dosages for restraint in these additional species, based on limited clinical data, are: Cercopithecus aethiops (grivet), Papio papio (guinea baboon) 10 to 12 mg/kg; Erythrocebus patas patas (patas monkey) 3 to 5 mg/kg; Hylobates lar (white-handed gibbon) 5 to 10 mg/kg; Lemur catta (ringtailed lemur) 7.5 to 10 mg/kg; Macaca fuscata (Japanese macaque) 5 mg/kg; Macaca speciosa (stumptailed macaque) and Miopithecus talapoin (mangrove monkey) 5 to 7.5 mg/kg; and Symphalangus syndactylus (siamangs) 5 to 7 mg/kg.

STORAGE INFORMATION

Store at or below 25°C (77°F). Protect from light. Do not use if precipitate appears. Use contents within 4 months of first puncture.

HOW SUPPLIED

KETASET (ketamine hydrochloride injection) is supplied as the hydrochloride in concentrations equivalent to ketamine base.

Each 10 mL vial contains 100 mg/mL.

Approved by FDA under NADA # 043-304
zoetis
Manufactured by:
Zoetis Manufacturing and Research Spain, S.L.
Girona, Spain
Distributed by:
Zoetis Inc.
Kalamazoo, MI 49007
Revised: June 2019
40027679

PRINCIPAL DISPLAY PANEL - 1000 mg Carton

Ketaset® CIII

(ketamine hydrochloride injection)

1000 mg/10 mL

(100 mg/mL)

Caution: Federal law restricts this drug to use by or on the order of a licensed veterinarian.

Net Contents: 10 mL

Approved by FDA under NADA # 043-304